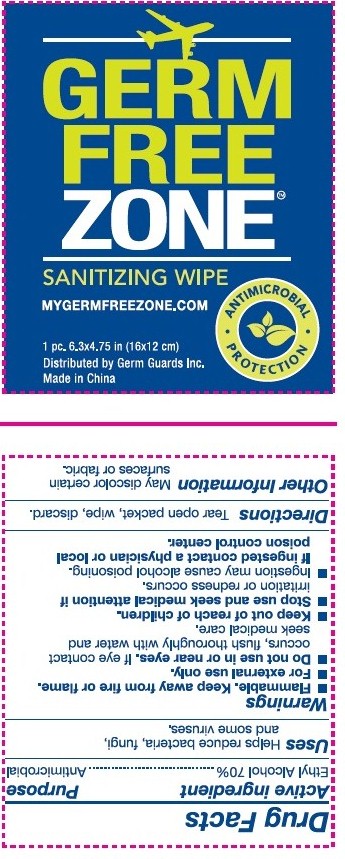 DRUG LABEL: Germ Free Zone Sanitizing Wipe
NDC: 71089-001 | Form: CLOTH
Manufacturer: Germ Guards Incorporated
Category: otc | Type: HUMAN OTC DRUG LABEL
Date: 20170601

ACTIVE INGREDIENTS: ALCOHOL .70 mL/1 mL
INACTIVE INGREDIENTS: GLYCERIN; WATER

DRUG FACTS

Active Ingredient

Ethyl Alcohol 70% (v/v)

Purpose

Antimicrobia

Uses:

Helps reduce becteria, fungl, and some viruses.

WARNINGS

For external use only.

DO NOT USE

- Flammable, keep away from heat and flame.
- Do not use in or near eyes. If eye contact occurs flush thoroughly with water and seek medical care.
- Avoid contact with broken skin.
- Stop use and seek medical attention if irritation and redness occurs.
- Ingestion may cause alcohol poisoning, if ingested contact a physician or local poison control center.

Keep out of reach of children.

In case of accidental ingestion, seekprofessional assistance or contact a Poison Control Center immediately.

Directions:

- Tear open packet, wipe, discard.

Inactive Ingredients:

purified water, Glycerol